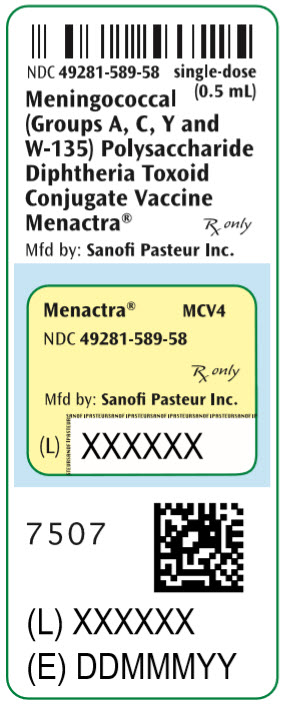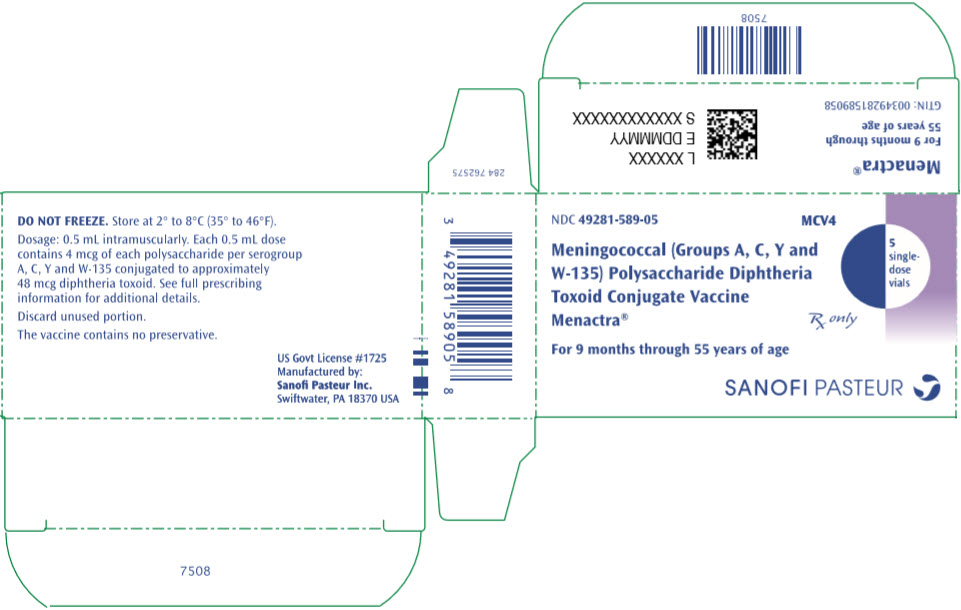 DRUG LABEL: Menactra
NDC: 49281-589 | Form: INJECTION, SOLUTION
Manufacturer: Sanofi Vaccines US Inc.
Category: other | Type: VACCINE LABEL
Date: 20260226

ACTIVE INGREDIENTS: NEISSERIA MENINGITIDIS GROUP A CAPSULAR POLYSACCHARIDE DIPHTHERIA TOXOID CONJUGATE ANTIGEN 4 ug/0.5 mL; NEISSERIA MENINGITIDIS GROUP C CAPSULAR POLYSACCHARIDE DIPHTHERIA TOXOID CONJUGATE ANTIGEN 4 ug/0.5 mL; NEISSERIA MENINGITIDIS GROUP Y CAPSULAR POLYSACCHARIDE DIPHTHERIA TOXOID CONJUGATE ANTIGEN 4 ug/0.5 mL; NEISSERIA MENINGITIDIS GROUP W-135 CAPSULAR POLYSACCHARIDE DIPHTHERIA TOXOID CONJUGATE ANTIGEN 4 ug/0.5 mL
INACTIVE INGREDIENTS: FORMALDEHYDE

HIGHLIGHTS OF PRESCRIBING INFORMATION

These highlights do not include all the information needed to use Menactra® safely and effectively. See full prescribing information for Menactra vaccine.
Menactra®, Meningococcal (Groups A, C, Y and W-135) Polysaccharide Diphtheria Toxoid Conjugate Vaccine
Solution for Intramuscular Injection
Initial U.S. Approval: 2005

1 INDICATIONS AND USAGE

Menactra is indicated for active immunization to prevent invasive meningococcal disease caused by Neisseria meningitidis serogroups A, C, Y and W-135. Menactra is approved for use in individuals 9 months through 55 years of age. Menactra does not prevent N meningitidis serogroup B disease. (1)

2 DOSAGE AND ADMINISTRATION

A 0.5 mL dose for intramuscular injection. (2)

Primary Vaccination:

- Children 9 through 23 months of age: Two doses, three months apart.
- Individuals 2 through 55 years of age: A single dose.

Booster Vaccination:

- A single booster dose may be given to individuals 15 through 55 years of age at continued risk for meningococcal disease, if at least 4 years have elapsed since the prior dose.

3 DOSAGE FORMS AND STRENGTHS

Solution supplied in 0.5 mL single-dose vials (3)

4 CONTRAINDICATIONS

- Severe allergic reaction (eg, anaphylaxis) after a previous dose of a meningococcal capsular polysaccharide-, diphtheria toxoid- or CRM197-containing vaccine, or to any component of Menactra. (4)

5 WARNINGS AND PRECAUTIONS

- Persons previously diagnosed with Guillain-Barré syndrome (GBS) may be at increased risk of GBS following receipt of Menactra. The decision to give Menactra should take into account the potential benefits and risks. (5.1)

6 ADVERSE REACTIONS

- Common (≥10%) solicited adverse events in infants and toddlers 9 and 12 months of age were injection site tenderness, erythema, and swelling; irritability, abnormal crying, drowsiness, appetite loss, vomiting, and fever. (6)
- Common (≥10%) solicited adverse events in individuals 2 through 55 years of age who received a single dose were injection site pain, redness, induration, and swelling; anorexia and diarrhea. Other common solicited adverse events were irritability and drowsiness (2-10 years of age), headache, fatigue, malaise, and arthralgia (11-55 years of age). (6)

To report SUSPECTED ADVERSE REACTIONS, contact Sanofi Pasteur Inc. at 1-800-822-2463 (1-800-VACCINE) or VAERS at 1-800-822-7967 or http://vaers.hhs.gov.

7 DRUG INTERACTIONS

- When Menactra and DAPTACEL® (Diphtheria and Tetanus Toxoids and Acellular Pertussis Vaccine Adsorbed) are to be administered to children 4 through 6 years of age, preference should be given to simultaneous administration of the 2 vaccines or administration of Menactra prior to DAPTACEL. Administration of Menactra one month after DAPTACEL has been shown to reduce meningococcal antibody responses to Menactra. (7.1)
- Pneumococcal antibody responses to some serotypes in Prevnar® (PCV7) were decreased following co-administration of Menactra and PCV7. (7.1)

8 USE IN SPECIFIC POPULATIONS

- Safety and effectiveness of Menactra have not been established in children younger than 9 months of age, pregnant women, nursing mothers, and adults older than 55 years of age. (8.1, 8.2, 8.4, 8.5)
- A pregnancy registry is available. Contact Sanofi Pasteur Inc. at 1-800-822-2463. (8.1)

FULL PRESCRIBING INFORMATION

1 INDICATIONS AND USAGE

Menactra®, Meningococcal (Groups A, C, Y and W-135) Polysaccharide Diphtheria Toxoid Conjugate Vaccine, is indicated for active immunization to prevent invasive meningococcal disease caused by Neisseria meningitidis serogroups A, C, Y and W-135. Menactra is approved for use in individuals 9 months through 55 years of age. Menactra does not prevent N meningitidis serogroup B disease.

2 DOSAGE AND ADMINISTRATION

2.1 Preparation for Administration

Menactra is a clear to slightly turbid solution. Parenteral drug products should be inspected visually for particulate matter and discoloration prior to administration, whenever solution and container permit. If any of these conditions exist, the vaccine should not be administered.

Withdraw the 0.5 mL dose of vaccine from the single-dose vial using a sterile needle and syringe.

2.2 Dose and Schedule

Menactra is administered as a 0.5 mL dose by intramuscular injection. Do not administer this product intravenously or subcutaneously.

Primary Vaccination:

- In children 9 through 23 months of age, Menactra is given as a 2-dose series three months apart.
- Individuals 2 through 55 years of age, Menactra is given as a single dose.

Booster Vaccination:

- A single booster dose may be given to individuals 15 through 55 years of age at continued risk for meningococcal disease, if at least 4 years have elapsed since the prior dose.

3 DOSAGE FORMS AND STRENGTHS

Menactra is a solution supplied in 0.5 mL single-dose vials. [See Description (11) for a complete listing of ingredients.]

4 CONTRAINDICATIONS

Severe allergic reaction (eg, anaphylaxis) after a previous dose of a meningococcal capsular polysaccharide-, diphtheria toxoid- or CRM197-containing vaccine, or to any component of Menactra [see Description (11)].

5 WARNINGS AND PRECAUTIONS

5.1 Guillain-Barré Syndrome

Persons previously diagnosed with Guillain-Barré syndrome (GBS) may be at increased risk of GBS following receipt of Menactra. The decision to give Menactra should take into account the potential benefits and risks.

GBS has been reported in temporal relationship following administration of Menactra (1) (2). The risk of GBS following Menactra vaccination was evaluated in a post-marketing retrospective cohort study [see Post-Marketing Experience (6.2)].

5.2 Preventing and Managing Allergic Vaccine Reactions

Prior to administration, the healthcare provider should review the immunization history for possible vaccine sensitivity and previous vaccination-related adverse reactions to allow an assessment of benefits and risks. Epinephrine and other appropriate agents used for the control of immediate allergic reactions must be immediately available should an acute anaphylactic reaction occur.

5.3 Altered Immunocompetence

- Reduced Immune Response
  Some individuals with altered immunocompetence, including some individuals receiving immunosuppressant therapy, may have reduced immune responses to Menactra.
- Complement Deficiency
  Persons with certain complement deficiencies and persons receiving treatment that inhibits terminal complement activation (for example, eculizumab) are at increased risk for invasive disease caused by N meningitidis, including invasive disease caused by serogroups A, C, Y and W-135, even if they develop antibodies following vaccination with Menactra [see Clinical Pharmacology (12)].

5.4 Limitations of Vaccine Effectiveness

Menactra may not protect all recipients.

5.5 Syncope

Syncope (fainting) has been reported following vaccination with Menactra. Procedures should be in place to prevent falling injury and manage syncopal reactions.

6 ADVERSE REACTIONS

6.1 Clinical Trials Experience

Because clinical trials are conducted under widely varying conditions, adverse reaction rates observed in the clinical trials of a vaccine cannot be directly compared to rates in the clinical trials of another vaccine and may not reflect the rates observed in practice.

Children 9 Through 12 Months of Age

The safety of Menactra was evaluated in four clinical studies that enrolled 3721 participants who received Menactra at 9 and 12 months of age. At 12 months of age these children also received one or more other recommended vaccines [Measles, Mumps, Rubella and Varicella Virus Vaccine Live (MMRV) or Measles, Mumps, and Rubella Virus Vaccine (MMR) and Varicella Virus Vaccine Live (V) each manufactured by Merck & Co., Inc., Pneumococcal 7-valent Conjugate Vaccine (Diphtheria CRM197 Protein) manufactured by Wyeth Pharmaceuticals Inc. (PCV7), Hepatitis A Vaccine manufactured by Merck & Co., Inc. (HepA). A control group of 997 children was enrolled at 12 months of age and received two or more childhood vaccines [MMRV (or MMR+V), PCV7, HepA] at 12 months of age [see Concomitant Vaccine Administration (14.3)]. Three percent of individuals received MMR and V, instead of MMRV, at 12 months of age.

The primary safety study was a controlled trial that enrolled 1256 children who received Menactra at 9 and 12 months of age. At 12 months of age these children received MMRV (or MMR+V), PCV7 and HepA. A control group of 522 children received MMRV, PCV7 and HepA. Of the 1778 children, 78% of participants (Menactra, N=1056; control group, N=322) were enrolled at United States (US) sites and 22% at a Chilean site. (Menactra, N=200; control group, N=200).

Individuals 2 Through 55 Years of Age

The safety of Menactra was evaluated in eight clinical studies that enrolled 10,057 participants aged 2-55 years who received Menactra and 5,266 participants who received Menomune® – A/C/Y/W-135, Meningococcal Polysaccharide Vaccine, Groups A, C, Y and W-135 Combined. There were no substantive differences in demographic characteristics between the vaccine groups. Among Menactra recipients 2-55 years of age 24.0%, 16.2%, 40.4% and 19.4% were in the 2-10, 11-14, 15-25 and 26-55-year age groups, respectively. Among Menomune – A/C/Y/W-135 recipients 2-55 years of age 42.3%, 9.3%, 30.0% and 18.5% were in the 2-10, 11-14, 15-25 and 26-55-year age groups, respectively. The three primary safety studies were randomized, active-controlled trials that enrolled participants 2-10 years of age (Menactra, N=1713; Menomune – A/C/Y/W-135, N=1519), 11-18 years of age (Menactra, N=2270; Menomune – A/C/Y/W-135, N=972) and 18-55 years of age (Menactra, N=1384; Menomune – A/C/Y/W-135, N=1170), respectively. Of the 3232 children 2-10 years of age, 68% of participants (Menactra, N=1164; Menomune – A/C/Y/W-135, N=1031) were enrolled at US sites and 32% (Menactra, N=549; Menomune – A/C/Y/W-135, N=488) of participants at a Chilean site. The median ages in the Chilean and US subpopulations were 5 and 6 years, respectively. All adolescents and adults were enrolled at US sites. As the route of administration differed for the two vaccines (Menactra given intramuscularly, Menomune – A/C/Y/W-135 given subcutaneously), study personnel collecting the safety data differed from personnel administering the vaccine.

Booster Vaccination Study

In an open-label trial conducted in the US, 834 individuals were enrolled to receive a single dose of Menactra 4-6 years after a prior dose. The median age of participants was 17.1 years at the time of the booster dose.

Safety Evaluation

Participants were monitored after each vaccination for 20 or 30 minutes for immediate reactions, depending on the study. Solicited injection site and systemic reactions were recorded in a diary card for 7 consecutive days after each vaccination. Participants were monitored for 28 days (30 days for infants and toddlers) for unsolicited adverse events and for 6 months post-vaccination for visits to an emergency room, unexpected visits to an office physician, and serious adverse events. Unsolicited adverse event information was obtained either by telephone interview or at an interim clinic visit. Information regarding adverse events that occurred in the 6-month post-vaccination time period was obtained via a scripted telephone interview.

Serious Adverse Events in All Safety Studies

Serious adverse events (SAEs) were reported during a 6-month time period following vaccinations in individuals 9 months through 55 years of age. In children who received Menactra at 9 months and at 12 months of age, SAEs occurred at a rate of 2.0% - 2.5%. In participants who received one or more childhood vaccine(s) (without co-administration of Menactra) at 12 months of age, SAEs occurred at a rate of 1.6% - 3.6%, depending on the number and type of vaccines received. In children 2-10 years of age, SAEs occurred at a rate of 0.6% following Menactra and at a rate of 0.7% following Menomune – A/C/Y/W-135. In adolescents 11 through 18 years of age and adults 18 years through 55 years of age, SAEs occurred at a rate of 1.0% following Menactra and at a rate of 1.3% following Menomune – A/C/Y/W-135. In adolescents and adults, SAEs occurred at a rate of 1.3% following booster vaccination with Menactra.

Solicited Adverse Events in the Primary Safety Studies

The most frequently reported solicited injection site and systemic adverse reactions within 7 days following vaccination in children 9 months and 12 months of age (Table 1) were injection site tenderness and irritability.

The most frequently reported solicited injection site and systemic adverse reactions in US children aged 2-10 years of age (Table 2) were injection site pain and irritability. Diarrhea, drowsiness, and anorexia were also common.

The most commonly reported solicited injection site and systemic adverse reactions in adolescents, ages 11-18 years (Table 3), and adults, ages 18-55 years (Table 4), after a single dose were injection site pain, headache and fatigue. Except for redness in adults, injection site reactions were more frequently reported after Menactra vaccination than after Menomune – A/C/Y/W-135 vaccination.

Table 1: Percentage of US Participants Reporting Solicited Adverse Reactions Within 7 Days Following Vaccine Administration at 9 Months and 12 Months of Age
 | Menactra at 9 months of age |  |  | Menactra + PCV7 [PCV7 (Prevnar®) = Pneumococcal 7-valent Conjugate Vaccine] + MMRV [MMRV (ProQuad®) = Measles, Mumps, Rubella and Varicella Virus Vaccine Live] + HepA [HepA (VAQTA®) = Hepatitis A Vaccine, Inactivated] at 12 months of age |  |  | PCV7+ MMRV+ HepA at 12 months of age
 | N [N = The number of participants with available data.] =998 - 1002 |  |  | N=898 - 908 |  |  | N=302 - 307
Reaction | Any | Grade 2 | Grade 3 | Any | Grade 2 | Grade 3 | Any | Grade 2 | Grade 3
Local/Injection Site
Tenderness [Grade 2: cries and protests when injection site is touched, Grade 3: cries when injected limb is moved, or the movement of the injected limb is reduced.]
Menactra Site | 37.4 | 4.3 | 0.6 | 48.5 | 7.5 | 1.3 | - | - | -
PCV7 Site | - | - | - | 45.6 | 9.4 | 1.6 | 45.7 | 8.3 | 0.3
MMRV Site | - | - | - | 38.9 | 7.1 | 1.0 | 43.0 | 5.2 | 0.0
HepA Site | - | - | - | 43.4 | 8.7 | 1.4 | 40.9 | 4.6 | 0.3
Erythema [Grade 2: ≥1.0 inches to <2.0 inches, Grade 3: ≥2.0 inches.]
Menactra Site | 30.2 | 2.5 | 0.3 | 30.1 | 1.3 | 0.1 | - | - | -
PCV7 Site | - | - | - | 29.4 | 2.6 | 0.2 | 32.6 | 3.0 | 0.7
MMRV Site | - | - | - | 22.5 | 0.9 | 0.3 | 33.2 | 5.9 | 0.0
HepA Site | - | - | - | 25.1 | 1.1 | 0.0 | 26.6 | 0.7 | 0.0
Swelling
Menactra Site | 16.8 | 0.9 | 0.2 | 16.2 | 0.9 | 0.1 | - | - | -
PCV7 Site | - | - | - | 19.5 | 1.3 | 0.4 | 16.6 | 1.3 | 0.7
MMRV Site | - | - | - | 12.1 | 0.4 | 0.1 | 14.1 | 0.3 | 0.0
HepA Site | - | - | - | 16.4 | 0.7 | 0.2 | 13.5 | 0.0 | 0.3
Systemic
Irritability [Grade 2: requires increased attention, Grade 3: inconsolable.] | 56.8 | 23.1 | 2.9 | 62.1 | 25.7 | 3.7 | 64.8 | 28.7 | 4.2
Abnormal crying [Grade 2: 1 to 3 hours, Grade 3: >3 hours.] | 33.3 | 8.3 | 2.0 | 40.0 | 11.5 | 2.4 | 39.4 | 10.1 | 0.7
Drowsiness [Grade 2: not interested in surroundings or did not wake up for a feed/meal, Grade 3: sleeping most of the time or difficult to wake up.] | 30.2 | 3.5 | 0.7 | 39.8 | 5.3 | 1.1 | 39.1 | 5.2 | 0.7
Appetite loss [Grade 2: missed 1 or 2 feeds/meals completely, Grade 3: refuses ≥3 feeds/meals or refuses most feeds/meals.] | 30.2 | 7.1 | 1.2 | 35.7 | 7.6 | 2.6 | 31.9 | 6.5 | 0.7
Vomiting [Grade 2: 2 to 5 episodes per 24 hours, Grade 3: ≥6 episodes per 24 hours or requiring parenteral hydration.] | 14.1 | 4.6 | 0.3 | 11.0 | 4.4 | 0.2 | 9.8 | 2.0 | 0.0
Fever [Grade 2: >38.5°C to ≤39.5°C, Grade 3: >39.5°C.] | 12.2 | 4.5 | 1.1 | 24.5 | 11.9 | 2.2 | 21.8 | 7.3 | 2.6

Table 2: Percentage of US Participants 2 Years Through 10 Years of Age Reporting Solicited Adverse Reactions Within 7 Days Following Vaccine Administration
 | Menactra |  |  | Menomune – A/C/Y/W-135
 | N [N = The total number of participants reporting at least one solicited reaction. The median age of participants was 6 years in both vaccine groups.] =1156 - 1157 |  |  | N=1027
Reaction | Any | Grade 2 | Grade 3 | Any | Grade 2 | Grade 3
Local/Injection Site
Pain [Grade 2: interferes with normal activities, Grade 3: disabling, unwilling to move arm.] | 45.0 | 4.9 | 0.3 | 26.1 | 2.5 | 0.0
Redness [Grade 2: 1.0-2.0 inches, Grade 3: >2.0 inches.] | 21.8 | 4.6 | 3.9 | 7.9 | 0.5 | 0.0
Induration | 18.9 | 3.4 | 1.4 | 4.2 | 0.6 | 0.0
Swelling | 17.4 | 3.9 | 1.9 | 2.8 | 0.3 | 0.0
Systemic
Irritability [Grade 2: 1-3 hours duration, Grade 3: >3 hours duration.] | 12.4 | 3.0 | 0.3 | 12.2 | 2.6 | 0.6
Diarrhea [Grade 2: 3-4 episodes, Grade 3: ≥5 episodes.] | 11.1 | 2.1 | 0.2 | 11.8 | 2.5 | 0.3
Drowsiness [Grade 2: interferes with normal activities, Grade 3: disabling, unwilling to engage in play or interact with others.] | 10.8 | 2.7 | 0.3 | 11.2 | 2.5 | 0.5
Anorexia [Grade 2: skipped 2 meals, Grade 3: skipped ≥3 meals.] | 8.2 | 1.7 | 0.4 | 8.7 | 1.3 | 0.8
Arthralgia [Grade 2: decreased range of motion due to pain or discomfort, Grade 3: unable to move major joints due to pain.] | 6.8 | 0.5 | 0.2 | 5.3 | 0.7 | 0.0
Fever [Oral equivalent temperature; Grade 2: 38.4°C to 39.4ºC, Grade 3: ≥39.5ºC.] | 5.2 | 1.7 | 0.3 | 5.2 | 1.7 | 0.2
Rash [These solicited adverse events were reported as present or absent only.] | 3.4 | - | - | 3.0 | - | -
Vomiting [Grade 2: 2 episodes, Grade 3: ≥3 episodes.] | 3.0 | 0.7 | 0.3 | 2.7 | 0.7 | 0.6
Seizure | 0.0 | - | - | 0.0 | - | -
Note: During the study Grade 1, Grade 2, and Grade 3 were collected as Mild, Moderate, and Severe respectively.

Table 3: Percentage of Participants 11 Years Through 18 Years of Age Reporting Solicited Adverse Reactions Within 7 Days Following Vaccine Administration With a Single Dose
 | Menactra |  |  | Menomune – A/C/Y/W-135
 | N [N = The number of participants with available data.] =2264 - 2265 |  |  | N=970
Reaction | Any | Grade 2 | Grade 3 | Any | Grade 2 | Grade 3
Local/Injection Site
Pain [Grade 2: interferes with or limits usual arm movement, Grade 3: disabling, unable to move arm.] | 59.2 [Denotes p <0.05 level of significance. The p-values were calculated for each category and severity using Chi Square test.] | 12.8 | 0.3 | 28.7 | 2.6 | 0.0
Induration [Grade 2: 1.0-2.0 inches, Grade 3: >2.0 inches.] | 15.7 | 2.5 | 0.3 | 5.2 | 0.5 | 0.0
Redness | 10.9 | 1.6 | 0.6 | 5.7 | 0.4 | 0.0
Swelling | 10.8 | 1.9 | 0.5 | 3.6 | 0.3 | 0.0
Systemic
Headache [Grade 2: interferes with normal activities, Grade 3: requiring bed rest.] | 35.6 | 9.6 | 1.1 | 29.3 | 6.5 | 0.4
Fatigue | 30.0 | 7.5 | 1.1 | 25.1 | 6.2 | 0.2
Malaise | 21.9 | 5.8 | 1.1 | 16.8 | 3.4 | 0.4
Arthralgia | 17.4 | 3.6 | 0.4 | 10.2 | 2.1 | 0.1
Diarrhea [Grade 2: 3-4 episodes, Grade 3: ≥5 episodes.] | 12.0 | 1.6 | 0.3 | 10.2 | 1.3 | 0.0
Anorexia [Grade 2: skipped 2 meals, Grade 3: skipped ≥3 meals.] | 10.7 | 2.0 | 0.3 | 7.7 | 1.1 | 0.2
Chills | 7.0 | 1.7 | 0.2 | 3.5 | 0.4 | 0.1
Fever [Oral equivalent temperature; Grade 2: 38.5°C to 39.4ºC, Grade 3: ≥39.5ºC.] | 5.1 | 0.6 | 0.0 | 3.0 | 0.3 | 0.1
Vomiting [Grade 2: 2 episodes, Grade 3: ≥3 episodes.] | 1.9 | 0.4 | 0.3 | 1.4 | 0.5 | 0.3
Rash [These solicited adverse events were reported as present or absent only.] | 1.6 | - | - | 1.4 | - | -
Seizure | 0.0 | - | - | 0.0 | - | -
Note: During the study Grade 1, Grade 2, and Grade 3 were collected as Mild, Moderate, and Severe respectively.

Table 4: Percentage of Participants 18 Years Through 55 Years of Age Reporting Solicited Adverse Reactions Within 7 Days Following Vaccine Administration With a Single Dose
 | Menactra |  |  | Menomune – A/C/Y/W-135
 | N [N = The number of participants with available data.] =1371 |  |  | N=1159
Reaction | Any | Grade 2 | Grade 3 | Any | Grade 2 | Grade 3
Local/Injection Site
Pain [Grade 2: interferes with or limits usual arm movement, Grade 3: disabling, unable to move arm.] | 53.9 [Denotes p <0.05 level of significance. The p-values were calculated for each category and severity using Chi Square test.] | 11.3 | 0.2 | 48.1 | 3.3 | 0.1
Induration [Grade 2: 1.0-2.0 inches, Grade 3: >2.0 inches.] | 17.1 | 3.4 | 0.7 | 11.0 | 1.0 | 0.0
Redness | 14.4 | 2.9 | 1.1 | 16.0 | 1.9 | 0.1
Swelling | 12.6 | 2.3 | 0.9 | 7.6 | 0.7 | 0.0
Systemic
Headache [Grade 2: interferes with normal activities, Grade 3: requiring bed rest.] | 41.4 | 10.1 | 1.2 | 41.8 | 8.9 | 0.9
Fatigue | 34.7 | 8.3 | 0.9 | 32.3 | 6.6 | 0.4
Malaise | 23.6 | 6.6 | 1.1 | 22.3 | 4.7 | 0.9
Arthralgia | 19.8 | 4.7 | 0.3 | 16.0 | 2.6 | 0.1
Diarrhea [Grade 2: 3-4 episodes, Grade 3: ≥5 episodes.] | 16.0 | 2.6 | 0.4 | 14.0 | 2.9 | 0.3
Anorexia [Grade 2: skipped 2 meals, Grade 3: skipped ≥3 meals.] | 11.8 | 2.3 | 0.4 | 9.9 | 1.6 | 0.4
Chills | 9.7 | 2.1 | 0.6 | 5.6 | 1.0 | 0.0
Vomiting [Grade 2: 2 episodes, Grade 3: ≥3 episodes.] | 2.3 | 0.4 | 0.2 | 1.5 | 0.2 | 0.4
Fever [Oral equivalent temperature; Grade 2: 39.0°C to 39.9ºC, Grade 3: ≥40.0ºC.] | 1.5 | 0.3 | 0.0 | 0.5 | 0.1 | 0.0
Rash [These solicited adverse events were reported as present or absent only.] | 1.4 | - | - | 0.8 | - | -
Seizure | 0.0 | - | - | 0.0 | - | -
Note: During the study Grade 1, Grade 2, and Grade 3 were collected as Mild, Moderate, and Severe respectively.

Solicited Adverse Events in a Booster Vaccination Study

For a description of the study design and number of participants, [see Clinical Trials Experience, Booster Vaccination Study (6.1)]. The most common solicited injection site and systemic reactions within 7 days of vaccination were pain (60.2%) and myalgia (42.8%), respectively. Overall rates of solicited injection site reactions and solicited systemic reactions were similar to those observed in adolescents and adults after a single Menactra dose. The majority of solicited reactions were Grade 1 or 2 and resolved within 3 days.

Adverse Events in Concomitant Vaccine Studies

Solicited Injection Site and Systemic Reactions when Given with Routine Pediatric Vaccines

For a description of the study design and number of participants, [see Clinical Trials Experience (6.1), Concomitant Vaccine Administration (14.3)]. In the primary safety study, 1378 US children were enrolled to receive Menactra alone at 9 months of age and Menactra plus one or more other routinely administered vaccines (MMRV, PCV7 and HepA) at 12 months of age (N=961). Another group of children received two or more routinely administered vaccines (MMRV, PCV7 and HepA) (control group, n=321) at 12 months of age. The frequency of occurrence of solicited adverse events is presented in Table 1. Participants who received Menactra and the concomitant vaccines at 12 months of age described above reported similar frequencies of tenderness, redness and swelling at the Menactra injection site and at the concomitant vaccine injection sites. Tenderness was the most frequent injection site reaction (48%, 39%, 46% and 43% at the Menactra, MMRV, PCV7 and HepA sites, respectively). Irritability was the most frequent systemic reaction, reported in 62% of recipients of Menactra plus concomitant vaccines, and 65% of the control group [see Concomitant Vaccine Administration (14.3)].

In a randomized, parallel group, US multi-center clinical trial conducted in children 4 through 6 years of age, Menactra was administered as follows: 30 days after concomitant DAPTACEL®, Diphtheria and Tetanus Toxoids and Acellular Pertussis Vaccine Adsorbed, (DTaP), manufactured by Sanofi Pasteur Limited + IPOL®, Poliovirus Vaccine Inactivated, (IPV), manufactured by Sanofi Pasteur SA [Group A]; concomitantly with DAPTACEL followed 30 days later by IPV [Group B]; concomitantly with IPV followed 30 days later by DAPTACEL [Group C]. Solicited injection site and systemic reactions were recorded in a diary card for 7 consecutive days after each vaccination. For all study groups, the most frequently reported solicited local reaction at the Menactra site was pain: 52.2%, 60.9% and 56.0% of participants in Groups A, B and C, respectively. For all study groups, the most frequently reported systemic reaction following the administration of Menactra alone or with the respective concomitant vaccines was myalgia: 24.2%, 37.3% and 26.7% of participants in Groups A, B and C, respectively. Fever >39.5ºC occurred at <1.0% in all groups [see Concomitant Vaccine Administration (14.3)].

Solicited Injection Site and Systemic Reactions when Given with Tetanus and Diphtheria Toxoid Adsorbed Vaccine

In a clinical study, rates of local and systemic reactions after Menactra and Tetanus and Diphtheria Toxoid Adsorbed (Td) vaccine manufactured by Sanofi Pasteur Inc. were compared [see Drug Interactions (7), and Concomitant Vaccine Administration (14.3) for study description]. Injection site pain was reported more frequently after Td vaccination than after Menactra vaccination (71% versus 53%). The overall rate of systemic adverse events was higher when Menactra and Td vaccines were given concomitantly than when Menactra was administered 28 days after Td vaccine (59% versus 36%). In both groups, the most common reactions were headache (Menactra + Td vaccine, 36%; Td vaccine + Placebo, 34%; Menactra alone, 22%) and fatigue (Menactra + Td vaccine, 32%; Td vaccine + Placebo, 29%; Menactra alone, 17%). Fever ≥40.0ºC occurred at ≤0.5% in all groups.

Solicited Injection Site and Systemic Reactions when Given with Typhoid Vi Polysaccharide Vaccine

In a clinical study, rates of local and systemic reactions after Menactra and Typhim Vi® [Typhoid Vi Polysaccharide Vaccine] (Typhoid), produced by Sanofi Pasteur SA were compared [see Drug Interactions (7) and Concomitant Vaccine Administration (14.3)] for a description of the concomitantly administered vaccine, study design and number of participants. More participants experienced pain after Typhoid vaccination than after Menactra vaccination (Typhoid + Placebo, 76% versus Menactra + Typhoid, 47%). The majority (70%-77%) of injection site solicited reactions for both groups at either injection site were reported as Grade 1 and resolved within 3 days post-vaccination. In both groups, the most common systemic reaction was headache (Menactra + Typhoid, 41%; Typhoid + Placebo, 42%; Menactra alone, 33%) and fatigue (Menactra + Typhoid, 38%; Typhoid + Placebo, 35%; Menactra alone, 27%). Fever ≥40.0ºC and seizures were not reported in either group.

6.2 Post-Marketing Experience

In addition to reports in clinical trials, worldwide voluntary adverse events reports received since market introduction of Menactra are listed below. This list includes serious events and/or events which were included based on severity, frequency of reporting or a plausible causal connection to Menactra. Because these events were reported voluntarily from a population of uncertain size, it is not possible to reliably estimate their frequency or establish a causal relationship to vaccination.

- Blood and Lymphatic System Disorders
  Lymphadenopathy
- Immune System Disorders
  Hypersensitivity reactions such as anaphylaxis/anaphylactic reaction, wheezing, difficulty breathing, upper airway swelling, urticaria, erythema, pruritus, hypotension
- Nervous System Disorders
  Guillain-Barré syndrome, paraesthesia, vasovagal syncope, dizziness, convulsion, facial palsy, acute disseminated encephalomyelitis, transverse myelitis
- Musculoskeletal and Connective Tissue Disorders
  Myalgia
- General Disorders and Administrative Site Conditions
  Large injection site reactions, extensive swelling of the injected limb (may be associated with erythema, warmth, tenderness or pain at the injection site).

Post-marketing Safety Study

The risk of GBS following receipt of Menactra was evaluated in a US retrospective cohort study using healthcare claims data from 9,578,688 individuals 11 through 18 years of age, of whom 1,431,906 (15%) received Menactra. Of 72 medical chart-confirmed GBS cases, none had received Menactra within 42 days prior to symptom onset. An additional 129 potential cases of GBS could not be confirmed or excluded due to absent or insufficient medical chart information. In an analysis that took into account the missing data, estimates of the attributable risk of GBS ranged from 0 to 5 additional cases of GBS per 1,000,000 vaccinees within the 6-week period following vaccination.

7 DRUG INTERACTIONS

7.1 Concomitant Administration with Other Vaccines

Menactra vaccine was concomitantly administered with Typhim Vi® [Typhoid Vi Polysaccharide Vaccine] (Typhoid) and Tetanus and Diphtheria Toxoids Adsorbed, For Adult Use (Td) vaccine, in individuals 18 through 55 and 11 through 17 years of age, respectively. In children 4 through 6 years of age, Menactra was co-administered with DAPTACEL, and in children younger than 2 years of age, Menactra was co-administered with one or more of the following vaccines: PCV7, MMR, V, MMRV, or HepA [see Clinical Studies (14) and Adverse Reactions (6)].

When Menactra and DAPTACEL are to be administered to children 4 through 6 years of age, preference should be given to simultaneous administration of the 2 vaccines or administration of Menactra prior to DAPTACEL. Administration of Menactra one month after DAPTACEL has been shown to reduce meningococcal antibody responses to Menactra. Data are not available to evaluate the immune response to Menactra administered to younger children following DAPTACEL or to Menactra administered to persons <11 years of age following other diphtheria toxoid-containing vaccines [see Clinical Studies (14.3)].

Pneumococcal antibody responses to some serotypes in PCV7 were decreased following co-administration of Menactra and PCV7 [see Concomitant Vaccine Administration (14.3)].

Do not mix Menactra with other vaccines in the same syringe. When Menactra is administered concomitantly with other injectable vaccines, the vaccines should be administered with different syringes and given at separate injection sites.

7.2 Immunosuppressive Therapies

Immunosuppressive therapies, including irradiation, antimetabolites, alkylating agents, cytotoxic drugs, and corticosteroids (used in greater than physiologic doses) may reduce the immune response to vaccines.

8 USE IN SPECIFIC POPULATIONS

8.1 Pregnancy

Pregnancy Exposure Registry

There is a pregnancy exposure registry that monitors pregnancy outcomes in women exposed to Menactra during pregnancy. To enroll in or obtain information about the registry, call Sanofi Pasteur at 1-800-822-2463.

Risk Summary

All pregnancies have a risk of birth defect, loss, or other adverse outcomes. In the US general population, the estimated background risk of major birth defects and miscarriage in clinically recognized pregnancies is 2% to 4% and 15% to 20%, respectively. There are no adequate and well-controlled studies of Menactra administration in pregnant women in the US. Available data suggest that rates of major birth defects and miscarriage in women who received Menactra 30 days prior to pregnancy or during pregnancy are consistent with estimated background rates.

A developmental toxicity study was performed in female mice given 0.1 mL (in divided doses) of Menactra prior to mating and during gestation (a single human dose is 0.5 mL). The study revealed no evidence of harm to the fetus due to Menactra [see Animal Data (8.1)].

Data

Human Data

A pregnancy registry spanning 11 years (2005-2016) included 222 reports of exposure to Menactra from 30 days before or at any time during pregnancy. Of these reports, 87 had known pregnancy outcomes available and were enrolled in the pregnancy registry prior to the outcomes being known. Outcomes among these prospectively followed pregnancies included 2 major birth defects and 6 miscarriages.

Animal Data

A developmental toxicity study was performed in female mice. The animals were administered 0.1 mL of Menactra (in divided doses) at each of the following time points: 14 days prior to mating, and on Days 6 and 18 of gestation (a single human dose is 0.5 mL). There were no vaccine-related fetal malformations or variations, and no adverse effects on pre-weaning development observed in the study.

8.2 Lactation

Risk Summary

The developmental and health benefits of breastfeeding should be considered along with the mother's clinical need for Menactra and any potential adverse effects on the breastfed child from Menactra. Data are not available to assess the effects of Menactra on the breastfed infant or on milk production/excretion.

8.4 Pediatric Use

Menactra is not approved for use in infants under 9 months of age. Available data show that infants administered three doses of Menactra (at 2, 4, and 6 months of age) had diminished responses to each meningococcal vaccine serogroup compared to older children given two doses at 9 and 12 months of age.

8.5 Geriatric Use

Safety and effectiveness of Menactra in adults older than 55 years of age have not been established.

11 DESCRIPTION

Menactra is a sterile, intramuscularly administered vaccine that contains N meningitidis serogroup A, C, Y and W-135 capsular polysaccharide antigens individually conjugated to diphtheria toxoid protein. N meningitidis A, C, Y and W-135 strains are cultured on Mueller Hinton agar (3) and grown in Watson Scherp (4) media containing casamino acid. The polysaccharides are extracted from the N meningitidis cells and purified by centrifugation, detergent precipitation, alcohol precipitation, solvent extraction and diafiltration. To prepare the polysaccharides for conjugation, they are depolymerized, derivatized, and purified by diafiltration. Diphtheria toxin is derived from Corynebacterium diphtheriae grown in modified culture medium containing hydrolyzed casein (5) and is detoxified using formaldehyde. The diphtheria toxoid protein is purified by ammonium sulfate fractionation and diafiltration. The derivatized polysaccharides are covalently linked to diphtheria toxoid and purified by serial diafiltration. The four meningococcal components, present as individual serogroup-specific glycoconjugates, compose the final formulated vaccine. No preservative or adjuvant is added during manufacture. Each 0.5 mL dose may contain residual amounts of formaldehyde of less than 2.66 mcg (0.000532%), by calculation. Potency of Menactra is determined by quantifying the amount of each polysaccharide antigen that is conjugated to diphtheria toxoid protein and the amount of unconjugated polysaccharide present.

Menactra is manufactured as a sterile, clear to slightly turbid liquid. Each 0.5 mL dose of vaccine is formulated in sodium phosphate buffered isotonic sodium chloride solution to contain 4 mcg each of meningococcal A, C, Y and W-135 polysaccharides conjugated to approximately 48 mcg of diphtheria toxoid protein carrier.

The vial stopper is not made with natural rubber latex.

12 CLINICAL PHARMACOLOGY

12.1 Mechanism of Action

The presence of bactericidal anti-capsular meningococcal antibodies has been associated with protection from invasive meningococcal disease (6) (7). Menactra induces the production of bactericidal antibodies specific to the capsular polysaccharides of serogroups A, C, Y and W-135.

13 NON-CLINICAL TOXICOLOGY

13.1 Carcinogenesis, Mutagenesis, Impairment of Fertility

Menactra has not been evaluated for carcinogenic or mutagenic potential, or for impairment of male fertility. A developmental animal toxicity study showed that Menactra had no effects on female fertility in mice [see Pregnancy (8.1)].

14 CLINICAL STUDIES

14.1 Efficacy

The serum bactericidal assay (SBA) used to test sera contained an exogenous complement source that was either human (SBA-H) or baby rabbit (SBA-BR). (8)

The response to vaccination following two doses of vaccine administered to children 9 and 12 months of age and following one dose of vaccine administered to children 2 through 10 years of age was evaluated by the proportion of participants having an SBA-H antibody titer of 1:8 or greater, for each serogroup. In individuals 11 through 55 years of age, the response to vaccination with a single dose of vaccine was evaluated by the proportion of participants with a 4-fold or greater increase in bactericidal antibody to each serogroup as measured by SBA-BR. For individuals 2 through 55 years of age, vaccine efficacy after a single dose was inferred from the demonstration of immunologic equivalence to a US-licensed meningococcal polysaccharide vaccine, Menomune – A/C/Y/W-135 vaccine as assessed by SBA.

14.2 Immunogenicity

Children 9 through 12 Months of Age

In a randomized, US, multi-center trial, children received Menactra at 9 months and 12 months of age. The first Menactra dose was administered alone, followed by a second Menactra dose given alone (N=404), or with MMRV (N=302), or with PCV7 (N=422). For all participants, sera were obtained approximately 30 days after last vaccination. There were no substantive differences in demographic characteristics between the vaccine groups. The median age range for administration of the first dose of Menactra was 278-279 days of age.

Table 5: Bactericidal Antibody Responses [Serum bactericidal assay with an exogenous human complement (SBA-H) source.] 30 Days Following a Second Dose of Menactra Administered Alone or Concomitantly Administered with MMRV or PCV7 at 12 Months of Age
 |  | Vaccinations administered at 12 months of age following a dose of Menactra at 9 months of age
 |  | Menactra |  | Menactra + MMRV |  | Menactra + PCV7
 |  | (N=272-277) [N=Number of participants with at least one valid serology result from a blood sample obtained between Days 30 to 44 post vaccination.] |  | (N=177-180) |  | (N=264-267)
Serogroup |  |  | (95% CI) [95% CIs for the proportions are calculated based on the Clopper-Pearson Exact method and normal approximation for that of the GMTs.] |  | (95% CI) |  | (95% CI)
A | % ≥1:8 [The proportion of participants achieving an SBA-H titer of at least 1:8 thirty days after the second dose of Menactra.] | 95.6 | (92.4; 97.7) | 92.7 | (87.8; 96.0) | 90.5 | (86.3; 93.8)
 | GMT | 54.9 | (46.8; 64.5) | 52.0 | (41.8; 64.7) | 41.0 | (34.6; 48.5)
C | % ≥1:8 | 100.0 | (98.7; 100.0) | 98.9 | (96.0; 99.9) | 97.8 | (95.2; 99.2)
 | GMT | 141.8 | (123.5; 162.9) | 161.9 | (136.3; 192.3) | 109.5 | (94.1; 127.5)
Y | %≥1:8 | 96.4 | (93.4; 98.2) | 96.6 | (92.8; 98.8) | 95.1 | (91.8; 97.4)
 | GMT | 52.4 | (45.4; 60.6) | 60.2 | (50.4; 71.7) | 39.9 | (34.4; 46.2)
W-135 | %≥1:8 | 86.4 | (81.8; 90.3) | 88.2 | (82.5; 92.5) | 81.2 | (76.0; 85.7)
 | GMT | 24.3 | (20.8; 28.3) | 27.9 | (22.7; 34.3) | 17.9 | (15.2; 21.0)

Administration of Menactra to children at 12 months and 15 months of age was evaluated in a US study. Prior to the first dose, 33.3% [n=16/48] of participants had an SBA-H titer ≥1:8 to Serogroup A, and 0-2% [n=0-1 of 50-51] to Serogroups C, Y and W-135. After the second dose, percentages of participants with an SBA-H titer ≥1:8 were: 85.2%, Serogroup A [n=46/54]; 100.0%, Serogroup C [n=54/54]; 96.3%, Serogroup Y [n=52/54]; 96.2%, Serogroup W-135 [n=50/52].

Individuals 2 through 55 Years of Age

Immunogenicity was evaluated in three comparative, randomized, US, multi-center, active controlled clinical trials that enrolled children (2 through 10 years of age), adolescents (11 through 18 years of age), and adults (18 through 55 years of age). Participants received a single dose of Menactra (N=2526) or Menomune – A/C/Y/W-135 (N=2317). For all age groups studied, sera were obtained before and approximately 28 days after vaccination. [Blinding procedures for safety assessments are described in Adverse Reactions (6).]

In each of the trials, there were no substantive differences in demographic characteristics between the vaccine groups, between immunogenicity subsets or the overall study population. In the study of children 2 through 10 years of age, the median age of participants was 3 years; 95% completed the study. In the adolescent trial, the median age for both groups was 14 years; 99% completed the study. In the adult trial, the median age for both groups was 24 years; 94% completed the study.

Immunogenicity in Children 2 through 10 Years of Age

Of 1408 enrolled children 2 through 10 years of age, immune responses evaluated in a subset of Menactra participants (2 through 3 years of age, n=52; 4-10 years of age, n=84) and Menomune – A/C/Y/W-135 participants (2 through 3 years of age, n=53; 4-10 years of age, n=84) were comparable for all four serogroups (Table 6).

Table 6: Comparison of Bactericidal Antibody Responses [Serum bactericidal assay with an exogenous human complement (SBA-H) source.] to Menactra and Menomune – A/C/Y/W-135 28 Days after Vaccination for a Subset of Participants 2 through 3 Years of Age and 4 through 10 Years of Age
 |  | Ages 2 through 3 Years |  |  |  | Ages 4 through 10 Years
 |  | Menactra |  | Menomune – A/C/Y/W-135 |  | Menactra |  | Menomune – A/C/Y/W-135
 |  | N [N=Number of subset participants with at least one valid serology result at Day 0 and Day 28.] =48-52 |  | N=50-53 |  | N=84 |  | N=84
Serogroup |  |  | (95% CI) [The 95% CI for the Geometric Mean Titer (GMT) was calculated based on an approximation to the normal distribution.] |  | (95% CI) |  | (95% CI) |  | (95% CI)
A | % ≥1:8 [The proportion of participants achieving an SBA-H titer of at least 1:8 was assessed using a 10% non-inferiority margin and a one-sided Type 1 error rate of 0.025.] | 73 | (59,84) | 64 | (50,77) | 81 | (71,89) | 55 | (44,66)
 | GMT | 10 | (8,13) | 10 | (7,12) | 19 | (14,26) | 7 | (6,9)
C | % ≥1:8 | 63 | (48,76) | 38 | (25,53) | 79 | (68,87) | 48 | (37,59)
 | GMT | 27 | (14,52) | 11 | (5,21) | 28 | (19,41) | 12 | (7,18)
Y | % ≥1:8 | 88 | (75,95) | 73 | (59,84) | 99 | (94,100) | 92 | (84,97)
 | GMT | 51 | (31,84) | 18 | (11,27) | 99 | (75,132) | 46 | (33,66)
W-135 | % ≥1:8 | 63 | (47,76) | 33 | (20,47) | 85 | (75,92) | 79 | (68,87)
 | GMT | 15 | (9,25) | 5 | (3,6) | 24 | (18,33) | 20 | (14,27)

In the subset of participants 2 through 3 years of age with undetectable pre-vaccination titers (ie, SBA-H titers <1:4 at Day 0), seroconversion rates (defined as the proportions of participants with SBA-H titers ≥1:8 by Day 28) were similar between the Menactra and Menomune – A/C/Y/W-135 recipients. Menactra participants achieved seroconversion rates of: 57%, Serogroup A (n=12/21); 62%, Serogroup C (n=29/47); 84%, Serogroup Y (n=26/31); 53%, Serogroup W-135 (n=20/38). The seroconversion rates for Menomune – A/C/Y/W-135 recipients were: 55%, Serogroup A (n=16/29); 30%, Serogroup C (n=13/43); 57%, Serogroup Y (n=17/30); 26%, Serogroup W-135 (n=11/43).

In the subset of participants 4 through 10 years of age with undetectable pre-vaccination titers (ie, SBA-H titers <1:4 at Day 0), seroconversion rates (defined as the proportions of participants with SBA-H titers ≥1:8 by Day 28) were similar between the Menactra and Menomune – A/C/Y/W-135 recipients. Menactra participants achieved seroconversion rates of: 69%, Serogroup A (n=11/16); 81%, Serogroup C (n=50/62); 98%, Serogroup Y (n=45/46); 69%, Serogroup W-135 (n=27/39). The seroconversion rates for Menomune – A/C/Y/W-135 recipients were: 48%, Serogroup A (n=10/21); 38%, Serogroup C (n=19/50); 84%, Serogroup Y (n=38/45); 68%, Serogroup W-135 (n=26/38).

Immunogenicity in Adolescents 11 through 18 Years of Age

Results from the comparative clinical trial conducted in 881 adolescents aged 11 through 18 years showed that the immune responses to Menactra and Menomune – A/C/Y/W-135 were similar for all four serogroups (Table 7).

In participants with undetectable pre-vaccination titers (ie, SBA-BR titers <1:8 at Day 0), seroconversion rates (defined as the proportions of participants achieving a ≥4-fold rise in SBA-BR titers by Day 28) were similar between the Menactra and Menomune – A/C/Y/W-135 recipients. Menactra participants achieved seroconversion rates of: 100%, Serogroup A (n=81/81); 99%, Serogroup C (n=153/155); 98%, Serogroup Y (n=60/61); 98%, Serogroup W-135 (n=161/164). The seroconversion rates for Menomune – A/C/Y/W-135 recipients were: 100%, Serogroup A (n=93/93); 99%, Serogroup C (n=151/152); 100%, Serogroup Y (n=47/47); 99%, Serogroup W-135 (n=138/139).

Immunogenicity in Adults 18 through 55 Years of Age

Results from the comparative clinical trial conducted in 2554 adults aged 18 through 55 years showed that the immune responses to Menactra and Menomune – A/C/Y/W-135 were similar for all four serogroups (Table 7).

Table 7: Comparison of Bactericidal Antibody Responses [Serum bactericidal assay with baby rabbit complement (SBA-BR).] to Menactra and Menomune – A/C/Y/W-135 28 Days after Vaccination for Participants 11 through 18 Years of Age and 18 through 55 Years of Age
 |  | Ages 11 through 18 Years |  |  |  | Ages 18 through 55 Years
 |  | Menactra |  | Menomune – A/C/Y/W-135 |  | Menactra |  | Menomune – A/C/Y/W-135
 |  | N [N=Number of subset participants with at least one valid serology result at Day 0 and Day 28.] =423 |  | N=423 |  | N=1280 |  | N=1098
Serogroup |  |  | (95% CI) [The 95% CI for the Geometric Mean Titer (GMT) was calculated based on an approximation to the normal distribution.] |  | (95% CI) |  | (95% CI) |  | (95% CI)
A | % ≥4-fold rise [Menactra was non-inferior to Menomune – A/C/Y/W-135. Non-inferiority was assessed by the proportion of participants with a 4-fold or greater rise in SBA-BR titer for N meningitidis serogroups A, C, Y and W-135 using a 10% non-inferiority margin and a one-sided Type I error rate of 0.05.] | 92.7 | (89.8, 95.0) | 92.4 | (89.5, 94.8) | 80.5 | (78.2, 82.6) | 84.6 | (82.3, 86.7)
A | GMT | 5483 | (4920, 6111) | 3246 | (2910, 3620) | 3897 | (3647, 4164) | 4114 | (3832, 4417)
C | % ≥4-fold rise | 91.7 | (88.7, 94.2) | 88.7 | (85.2, 91.5) | 88.5 | (86.6, 90.2) | 89.7 | (87.8, 91.4)
C | GMT | 1924 | (1662, 2228) | 1639 | (1406, 1911) | 3231 | (2955, 3533) | 3469 | (3148, 3823)
Y | % ≥4-fold rise | 81.8 | (77.8, 85.4) | 80.1 | (76.0, 83.8) | 73.5 | (71.0, 75.9) | 79.4 | (76.9, 81.8)
Y | GMT | 1322 | (1162, 1505) | 1228 | (1088, 1386) | 1750 | (1597, 1918) | 2449 | (2237, 2680)
W-135 | % ≥4-fold rise | 96.7 | (94.5, 98.2) | 95.3 | (92.8, 97.1) | 89.4 | (87.6, 91.0) | 94.4 | (92.8, 95.6)
W-135 | GMT | 1407 | (1232, 1607) | 1545 | (1384, 1725) | 1271 | (1172, 1378) | 1871 | (1723, 2032)

In participants with undetectable pre-vaccination titers (ie, SBA-BR titers <1:8 at Day 0), seroconversion rates (defined as the proportions of participants achieving a ≥4-fold rise in SBA-BR titers by Day 28) were similar between the Menactra and Menomune – A/C/Y/W-135 recipients. Menactra participants achieved seroconversion rates of: 100%, Serogroup A (n=156/156); 99%, Serogroup C (n=343/345); 91%, Serogroup Y (n=253/279); 97%, Serogroup W-135 (n=360/373). The seroconversion rates for Menomune – A/C/Y/W-135 recipients were: 99%, Serogroup A (n=143/144); 98%, Serogroup C (n=297/304); 97%, Serogroup Y (n=221/228); 99%, Serogroup W-135 (n=325/328).

Immunogenicity in Adolescents and Adults Following Booster Vaccination

For a description of the study design and number of participants, [see Clinical Trials Experience, Booster Vaccination Study (6.1).] Prior to revaccination, the percentage of participants (n=781) with an SBA-H titer ≥1:8 were 64.5%, 44.2%, 38.7%, and 68.5% for Serogroups A, C, Y and W-135, respectively. Among the subset of trial participants (n=112) for whom SBA-H responses at Day 6 were assessed, 86.6%, 91.1%, 94.6%, and 92.0% achieved a ≥4-fold rise in SBA-H titer for Serogroups A, C, Y and W-135, respectively. The proportions of participants (n=781) who achieved a ≥4-fold rise in SBA-H titer by Day 28 were 95.0%, 95.3%, 97.1%, and 96% for Serogroups A, C, Y and W-135, respectively. The proportions of participants who achieved an SBA-H titer ≥1:8 by Day 28 were >99% for each serogroup.

14.3 Concomitant Vaccine Administration

MMRV (or MMR + V) or PCV7

In a US, active-controlled trial, 1179 children received Menactra at 9 months and 12 months of age. At 12 months of age these children received Menactra concomitantly with MMRV (N=616), or MMR + V (N=48), or PCV7 (N=250). Another group of 12-month old children received MMRV + PCV7 (N=485). Sera were obtained approximately 30 days after the last vaccinations. Measles, mumps, rubella and varicella antibody responses among children who received Menactra and MMRV (or MMR and V) were comparable to corresponding antibody responses among children who received MMRV and PCV7.

When Menactra was given concomitantly with PCV7, the non-inferiority criteria for comparisons of pneumococcal IgG GMCs (upper limit of the two-sided 95% CI of the GMC ratio ≤2) were not met for 3 of 7 serotypes (4, 6B, 18C). In a subset of participants with available sera, pneumococcal opsonophagocytic assay GMT data were consistent with IgG GMC data.

Td Vaccine

In a double-blind, randomized, controlled trial, 1021 participants aged 11 through 17 years received Td vaccine and Menactra concomitantly (N=509), or Td vaccine followed one month later by Menactra (N=512). Sera were obtained approximately 28 days after each respective vaccination. The proportions of participants with a 4-fold or greater increase in SBA-BR titer to meningococcal Serogroups C, Y and W-135 were higher when Menactra was given concomitantly with Td vaccine (86%-96%) than when Menactra was given one month following Td vaccine (65%-91%). Anti-tetanus and anti-diphtheria antibody responses were similar in both study groups.

Typhim Vi

In a double-blind, randomized, controlled trial, 945 participants aged 18 through 55 years received Typhim Vi and Menactra concomitantly (N=469), or Typhim Vi followed one month later by Menactra (N=476). Sera were obtained approximately 28 days after each respective vaccination. The antibody responses to Menactra and to Typhim Vi components were similar in both study groups.

DAPTACEL and IPV

In a randomized, parallel group, US multi-center clinical trial conducted in children 4 through 6 years of age, Menactra was administered as follows: 30 days after concomitant DTaP (DAPTACEL®, Sanofi Pasteur Limited) + IPV (IPOL®, Sanofi Pasteur SA) [Group A]; concomitantly with DAPTACEL followed 30 days later by IPV [Group B]; concomitantly with IPV followed 30 days later by DAPTACEL [Group C]. Sera were obtained approximately 30 days after each respective vaccination [see Clinical Trials Experience (6.1)].

When Menactra was administered 30 days after DAPTACEL (and IPV) [Group A], significantly lower SBA-H GMTs to all 4 meningococcal serogroups were observed compared to Menactra (and IPV) administered 30 days prior to DAPTACEL [Group C]. When Menactra was administered concomitantly with DAPTACEL [Group B], SBA-H GMTs to meningococcal serogroups A, C, and W-135 were non-inferior to those observed after Menactra (and IPV) [Group C]. The non-inferiority criterion was marginally missed for meningococcal serogroup Y. Non-inferiority of SBA-H GMTs following concomitant administration of Menactra and DAPTACEL compared to those after concomitant Menactra and IPV was concluded if the upper limit of the 2-sided 95% CI of (GMTGroup C divided by GMTGroup B) computed separately for each of the serogroups was <2.

The respective SBA-H GMTs and proportion (%) of Group A, B, and C study participants achieving an SBA-H titer of ≥1:8 are displayed in Table 8.

Table 8: Bactericidal Antibody Responses [Serum bactericidal assay with an exogenous human complement (SBA-H) source.] 30 Days Following Menactra Administered Alone or Concomitantly with DAPTACEL or IPV
 |  | Vaccines administered at Visit 1 and 30 days later at Visit 2
 | Visit 1 Visit 2 | Group A DAPTACEL + IPV Menactra |  | Group B Menactra + DAPTACEL IPV |  | Group C Menactra + IPV DAPTACEL
 |  | (N=250) [N=Total number of the subjects in the study population per group.] |  | (N=238) |  | (N=121)
Serogroup |  |  | (95% CI) [95% CIs for the proportions are calculated based on the Clopper-Pearson Exact method and normal approximation for that of the GMTs.] |  | (95% CI) |  | (95% CI)
A | % ≥1:8 [The proportion of participants achieving an SBA-H titer of at least 1:8, 30 days after Menactra.] | 49.6 | (41.0; 58.3) | 67.2 | (58.4; 75.1) | 64.4 | (54.4; 73.6)
A | GMT | 6.7 | (5.7; 8.0) | 10.8 | (8.7; 13.3) | 10.4 | (8.1; 13.3)
C | % ≥1:8 | 20.3 | (13.9; 28.0) | 50.4 | (41.5; 59.2) | 50.5 | (40.5; 60.5)
C | GMT | 3.3 | (2.7; 3.9) | 8.1 | (6.3; 10.5) | 7.8 | (5.8; 10.7)
Y | %≥1:8 | 44.2 | (35.8; 52.9) | 80.2 | (72.3; 86.6) | 88.5 | (80.7; 93.9)
Y | GMT | 6.5 | (5.1; 8.2) | 18.1 | (14.2; 22.9) | 26.2 | (20.0; 34.4)
W-135 | %≥1:8 | 55.1 | (46.4; 63.5) | 87.8 | (80.9; 92.9) | 82.7 | (74.0; 89.4)
W-135 | GMT | 8.4 | (6.7; 10.6) | 22.8 | (18.5; 28.1) | 21.7 | (16.6; 28.4)

When Menactra was administered concomitantly with DAPTACEL, antibody responses to three of the pertussis antigens (pertussis toxin, filamentous hemagglutinin, and pertactin) (GMCs), tetanus toxin (% participants with antibody concentrations ≥1.0 IU/mL), and diphtheria toxin (% participants with antibody concentrations ≥1.0 IU/mL) were non-inferior to those observed after DAPTACEL and IPV. The pertussis anti-fimbriae GMCs were marginally lower when Menactra and DAPTACEL were administered concomitantly.

15 REFERENCES

1 CDC. Guillain-Barré syndrome among recipients of Menactra® meningococcal conjugate vaccine-United States, June 2005-September 2006. MMWR Morb Mortal Wkly Rep 2006;55:1120-1124. Erratum in: MMWR Morb Mortal Wkly Rep 2006;55(43):1177.
2 Harvard Medical School/Harvard Pilgrim Health Care Institute. Risk of Guillain-Barré Syndrome Following Meningococcal Conjugate (MCV4) Vaccination. Final Study Report, Revised March 11, 2010.
3 Mueller JH, et al. A protein-free medium for primary isolation of the gonococcus and meningococcus. Proc Soc Exp Biol Med 1941;48:330-333.
4 Watson RG, et al. The specific hapten of group C (group IIa) meningococcus. I. Preparation and immunological behavior. J Immunol 1958;81:331-336.
5 Mueller JH, et al. Production of diphtheria toxin of high potency (100 Lf) on a reproducible medium. J Immunol 1941;40:21-32.
6 Mäkelä PH, et al. Evolution of conjugate vaccines. Expert Rev Vaccines 2002;1:399-410.
7 Goldschneider I, et al. Human immunity to the meningococcus. I. The role of humoral antibodies. J Exp Med 1969;129:1307-1326.
8 Maslanka SE, et al. Standardization and a multilaboratory comparison of Neisseria meningitidis serogroup A and C serum bactericidal assays. Clin and Diag Lab Immunol 1997;4:156-167.

16 HOW SUPPLIED/STORAGE AND HANDLING

16.1 How Supplied

- Single-dose vial, 0.5 mL (NDC 49281-589-58). Supplied as a package of 5 vials (NDC 49281-589-05).

16.2 Storage and Handling

Store at 2° to 8°C (35° to 46°F). DO NOT FREEZE. Frozen/previously frozen product should not be used. Do not use after the expiration date.

Discard any unused portion.

17 PATIENT COUNSELING INFORMATION

Vaccine Information Statements are required by the National Childhood Vaccine Injury Act of 1986 to be given prior to immunization to the patient, parent, or guardian. These materials are available free of charge at the Centers for Disease Control and Prevention (CDC) website (www.cdc.gov/vaccines).

Inform the patients, parents or guardians about:

- Potential benefits and risks of immunization with Menactra.
- Potential for adverse reactions that have been temporally associated with administration of Menactra or other vaccines containing similar components.
- Reporting any adverse reactions to their healthcare provider.
- The Sanofi Pasteur Inc. Pregnancy Registry, as appropriate [see Pregnancy (8.1)].

Menactra, DAPTACEL, Menomune, IPOL, and Typhim Vi are registered trademarks of Sanofi, its affiliates and subsidiaries.
Prevnar is a registered trademark of Wyeth LLC.
ProQuad and VAQTA are registered trademarks of Merck & Co., Inc.

Manufactured by:
Sanofi Pasteur Inc.
Swiftwater, PA 18370 USA

PRINCIPAL DISPLAY PANEL - 0.5 mL Vial Label

NDC 49281-589-58
single-dose
(0.5 mL)

Meningococcal
(Groups A, C, Y and
W-135) Polysaccharide
Diphtheria Toxoid
Conjugate Vaccine
Menactra®
Rx only
Mfd by: Sanofi Pasteur Inc.

Menactra®
MCV4

NDC 49281-589-58

Rx only

Mfd by: Sanofi Pasteur Inc.

(L)

7507

(L) XXXXXX

(E) DDMMMYY

PRINCIPAL DISPLAY PANEL - 5 Vial Package

NDC 49281-589-05

MCV4

Meningococcal (Groups A, C, Y and
W-135) Polysaccharide Diphtheria
Toxoid Conjugate Vaccine

5
single-
dose
vials

Menactra®

Rx only

For 9 months through 55 years of age

SANOFI PASTEUR